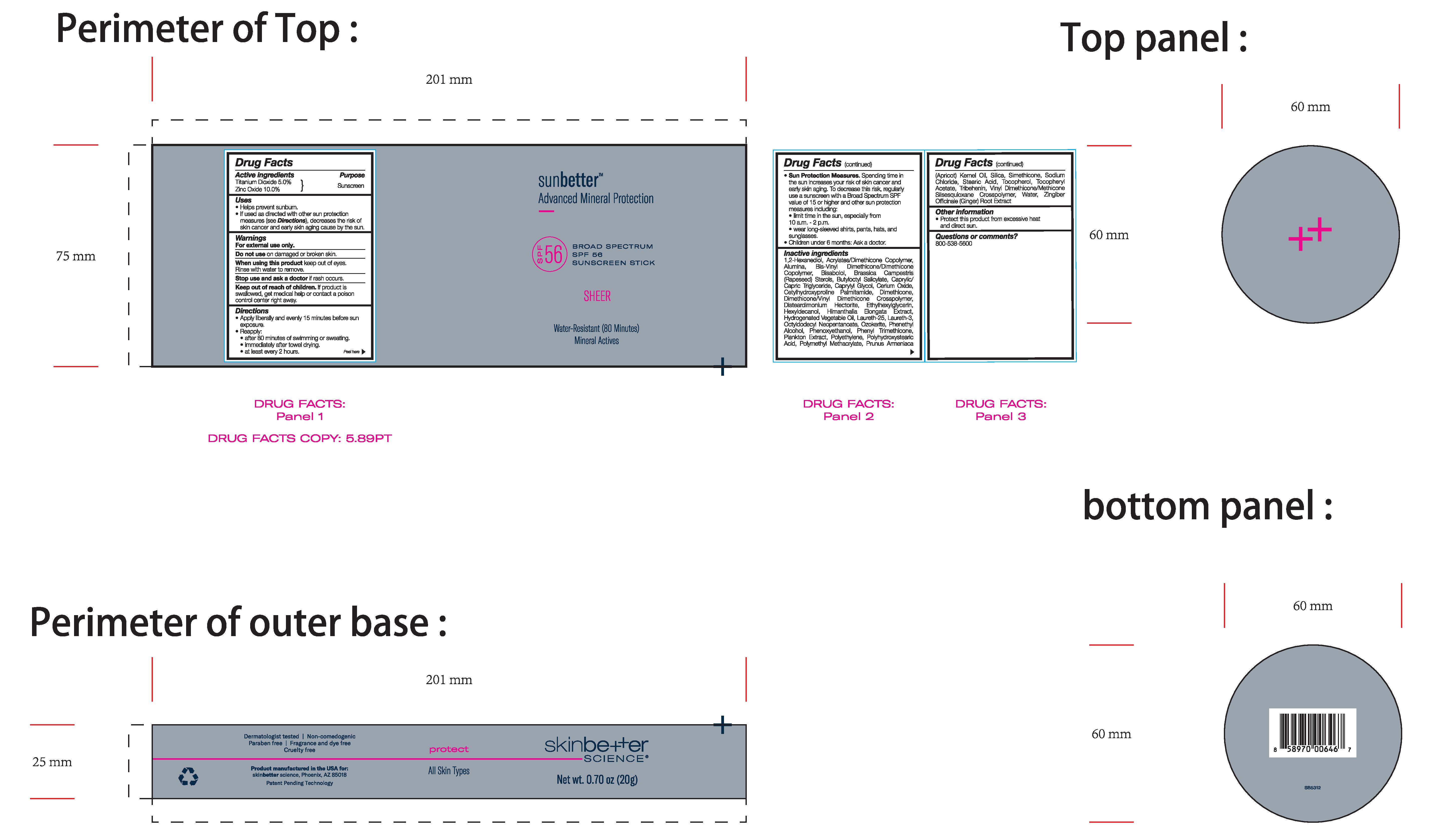 DRUG LABEL: sunbetter Broad Spectrum SPF 56 Sunscreen Stick Sheer
NDC: 73291-0002 | Form: STICK
Manufacturer: SKINBETTER SCIENCE LLC
Category: otc | Type: HUMAN OTC DRUG LABEL
Date: 20250106

ACTIVE INGREDIENTS: ZINC OXIDE 100 mg/1 g; TITANIUM DIOXIDE 50 mg/1 g
INACTIVE INGREDIENTS: ALUMINUM OXIDE; RAPESEED STEROL; BUTYLOCTYL SALICYLATE; CETYLHYDROXYPROLINE PALMITAMIDE; LAURETH-25; PHENOXYETHANOL; POLY(METHYL METHACRYLATE; 450000 MW); .ALPHA.-TOCOPHEROL, DL-; PHENYL TRIMETHICONE; HIGH DENSITY POLYETHYLENE; SILICON DIOXIDE; VINYL DIMETHICONE/METHICONE SILSESQUIOXANE CROSSPOLYMER; POLYHYDROXYSTEARIC ACID (2300 MW); 1,2-HEXANEDIOL; DIMETHICONE METHACRYLATE (3000 MW); HIMANTHALIA ELONGATA; CORN OIL; LAURETH-3; CERESIN; PHENYLETHYL ALCOHOL; APRICOT KERNEL OIL; SODIUM CHLORIDE; STEARIC ACID; ALPHA-TOCOPHEROL ACETATE; TRIBEHENIN; WATER; GINGER; ETHYLHEXYLGLYCERIN; .ALPHA.-BISABOLOL, (+/-)-; MEDIUM-CHAIN TRIGLYCERIDES; CAPRYLYL GLYCOL; CERIC OXIDE; DIMETHICONE; HEXYLDECANOL; DISTEARDIMONIUM HECTORITE; OCTYLDODECYL NEOPENTANOATE; DIMETHICONE/VINYL DIMETHICONE CROSSPOLYMER (SOFT PARTICLE)

sunbetter SHEER SPF 56 Sunscreen Stick

Drug Facts

Active ingredients

Titanium Dioxide 5.0%

Zinc Oxide 10.0%

Purpose

Sunscreen

Uses

- Helps prevent sunburn.
- If used as directed with other sun protection measures (see Directions), decreases the risk of skin cancer and early skin aging caused by the sun.

Warnings

For external use only.

Do not use on damaged or broken skin.

When using this product keep out of eyes. Rinse with water to remove.

Stop use and ask a doctor if rash occurs.

Keep out of reach of children. If swallowed, get medical help or contact a Poison Control Center right away.

Directions

- Sun Protection Measures. Spending time in the sun ircreases your risk of skin cancer and early skin aging. To decrease this risk, regularly use a sunscreen with a Broad Spectrum SPF value of 15 or higher and other sun protection measures including:
- limit time in the sun, especially from 10 a.m. - 2 p.m.
- wear long-sleeved shirts, pants, hats, and sunglasses.
- Children under 6 months: Ask a doctor.

DOSAGE AND ADMINISTRATION

Apply liberally and evenly 15 minutes before sun exposure.

Reapply:

after 80 minutes of swimming or sweating.

immediately after towel drying.

at least every 2 hours.

use a water resistant sunscreen if swimming or sweating.

Inactive ingredients

1,2-Hexanediol, Acrylates/Dimethicone Copolymer, Alumina, Bis-Vinyl Dimethicone/Dimethicone Copolymer, Bisabolol, Brassica Campestris (Rapeseed) Sterols, Butyloctyl Salicylate, Caprylic/Capric Triglyceride, Caprylyl Glycol, Cerium Oxide, Cetylhydroxyproline Palmitamide, Dimethicone, Dimethicone/Vinyl Dimethicone Crosspolymer, Disteardimonium Hectorite, Ethylhexylglycerin, Hexyldecanol, Himanthalia Elongata Extract, Hydrogenated Vegetable Oil, Laureth-25, Laureth-3, Octyldodecyl Neopentanoate, Ozokerite, Phenethyl Alcohol, Phenoxyethanol, Phenyl Trimethicone, Plankton Extract, Polyethylene, Polyhydroxystearic Acid, Polymethyl Methacrylate, Prunus Armeniaca (Apricot) Kernel Oil, Silica, Simethicone, Sodium Chloride, Stearic Acid, Tocopherol, Tocopheryl Acetate, Tribehenin, Vinyl Dimethicone/Methicone Silsesquioxane Crosspolymer, Water, Zingiber Officinale (Ginger) Root Extract.

Other information

Protect this product from excessive heat and direct sun.

Questions or comments?

800-538-5600

Principal Display Panel

sunbetter™
Advanced Mineral Protection

BROAD SPECTRUM

SPF 56

SUNSCREEN STICK

SHEER

Water-Resistant (80 Minutes)
Mineral Actives

skinbetter science®

Net wt. 0.70 oz (20 g)